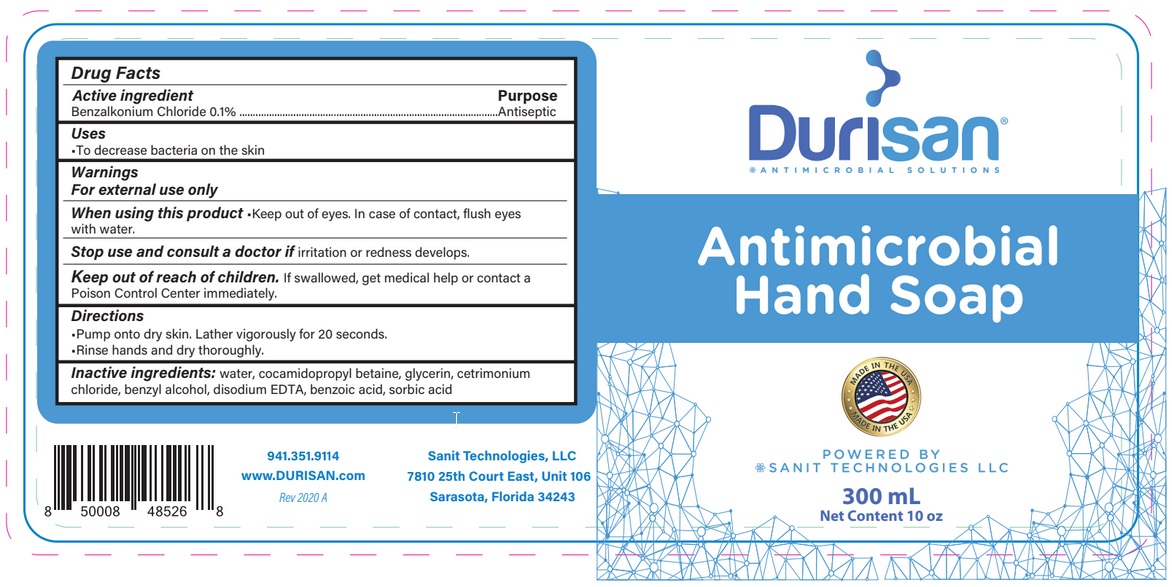 DRUG LABEL: Durisan
NDC: 71120-117 | Form: LIQUID
Manufacturer: Sanit Technologies LLC
Category: otc | Type: HUMAN OTC DRUG LABEL
Date: 20201202

ACTIVE INGREDIENTS: BENZALKONIUM CHLORIDE 1 mg/1 mL
INACTIVE INGREDIENTS: WATER; COCAMIDOPROPYL BETAINE; GLYCERIN; CETRIMONIUM CHLORIDE; BENZYL ALCOHOL; EDETATE DISODIUM ANHYDROUS; BENZOIC ACID; SORBIC ACID

Active Ingredient

Benzalkonium Chloride 0.1%

Purpose

Antiseptic

Use

To decrease bacteria on the skin.

Warnings

For external use only.

When using this product keep out of eyes. In case of contact eyes with water.

Stop use and consult a doctor if irritation or redness develops.

Keep out of reach of children. If swallowed, get medical help or contact a Poison Control Center right away.

Directions

- Pump onto dry skin. Lather vigorously for 20 seconds.
- Rinse hands and dry thoroughly.

Inactive ingredients

Water, cocamidopropyl betaine, glycerin, cetrimonium chloride, benzyl alcohol, disodium EDTA, benzoic acid, sorbic acid